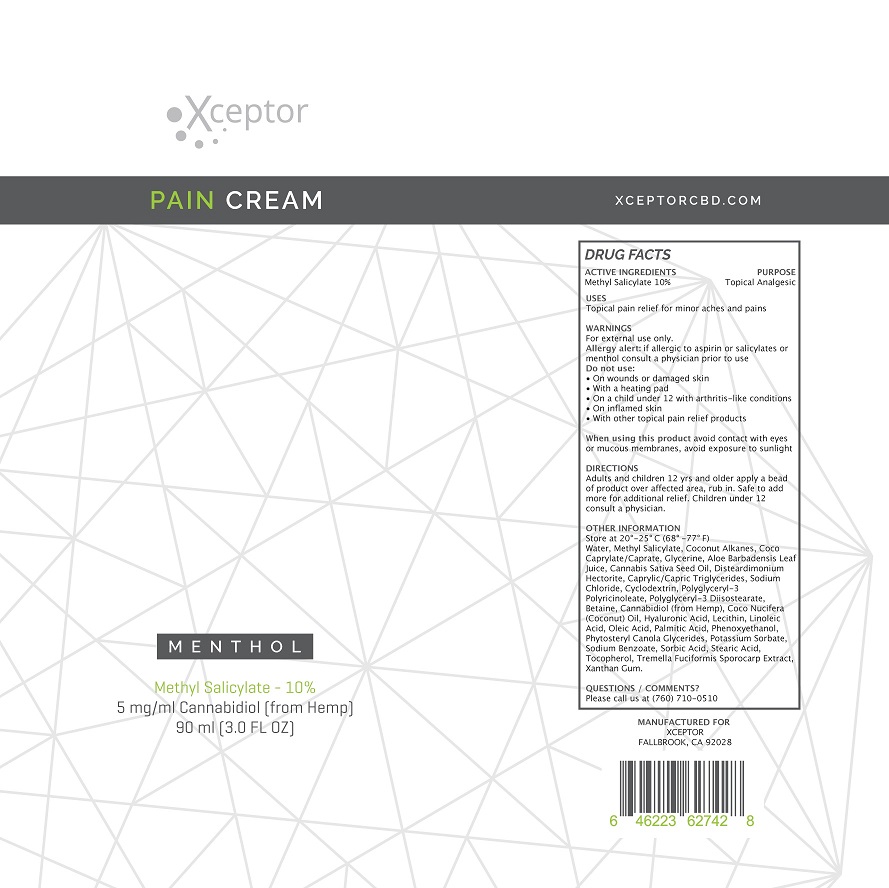 DRUG LABEL: XCEPTOR PAIN
NDC: 72519-101 | Form: CREAM
Manufacturer: XCEPTOR LLC
Category: otc | Type: HUMAN OTC DRUG LABEL
Date: 20200715

ACTIVE INGREDIENTS: METHYL SALICYLATE 10 g/100 mL
INACTIVE INGREDIENTS: WATER; COCONUT ALKANES; COCO-CAPRYLATE/CAPRATE; GLYCERIN; ALOE VERA LEAF; CANNABIS SATIVA SEED OIL; DISTEARDIMONIUM HECTORITE; MEDIUM-CHAIN TRIGLYCERIDES; SODIUM CHLORIDE; BETADEX; POLYGLYCERYL-3 RICINOLEATE; POLYGLYCERYL-3 DIISOSTEARATE; BETAINE; CANNABIDIOL; COCONUT OIL; HYALURONIC ACID; LECITHIN, SUNFLOWER; LINOLEIC ACID; OLEIC ACID; PALMITIC ACID; PHENOXYETHANOL; CANOLA OIL; POTASSIUM SORBATE; SODIUM BENZOATE; SORBIC ACID; STEARIC ACID; TOCOPHEROL; TREMELLA FUCIFORMIS FRUITING BODY; XANTHAN GUM

XCEPTOR PAIN CREAM

ACTIVE INGREDIENTS

METHYL SALICYLATE 10%

PURPOSE

TOPICAL ANALGESIC

USES

TOPICAL PAIN RELIEF FOR MINOR ACHES AND PAINS.

WARNINGS

FOR EXTERNAL USE ONLY.

ALLERGY ALERT: IF ALLERGIC TO ASPERIN OR SALICYLATES OR MENTHOL CONSULT A PHYSICIAN PRIOR TO USE.

DO NOT USE:

- ON WOUNDS OR DAMAGED SKIN
- WITH A HEATING PAD
- ON A CHILD UNDER 12 WITH ARTHRITIS-LIKE CONDITIONS
- ON INFLAMED SKIN
- WITH OTHER TOPICAL PAIN RELIEF PRODUCTS

WHEN USING THIS PRODUCT AVOID CONTACT WITH EYES OR MUCOUS MEMBRANES, AVOID EXPOSURE TO SUNLIGHT.

KEEP OUT OF REACH OF CHILDREN.

DIRECTIONS

ADULTS AND CHILDREN 12 YRS AND OLDER APPLY A BEAD OF PRODUCT OVER AFFECTED AREA, RUB IN. SAFE TO ADD MORE FOR ADDITIONAL RELIEF. CHILDREN UNDER 12 CONSULT A PHYSICIAN.

OTHER INFORMATION

STORE AT 20° - 25°C (68°-77°F)

INACTIVE INGREDIENTS

WATER, COCONUT ALKANES, COC-CAPRYLATE/CAPRATE, GLYCERINE, ALOE BARBADENSIS LEAF JUICE, CANNABIS SATIVA SEED OIL, DISTEARDIMONIUM HECTORITE, CAPRYLIC/CAPRIC TRIGLYCERIDES, SODIUM CHLORIDE, CYCLODEXTRIN, POLYGLYCERYL-3 POLYRICINOLEATE, POLYGLYCERYL-3 DIISOSTEARATE, BETAINE, CANNABIDOIL (FROM HEMP), COCOS NUCIFERA (COCONUT) OIL, HYALURONIC ACID, LECITHIN, LINOLEIC ACID, OLEIC ACID, PALMITIC ACID, PHENOXYETHANOL, PHYTOSTEARYL CANOLA GLYCERIDES, POTASSIUM SORBATE, SODIUM BENZOATE, SORBIC ACID, STEARIC ACID, TOCOPHEROL, TREMELLA FUCIFORMIS SPOROCARP EXTRACT, XANTHAN GUM.

QUESTIONS / COMMENTS?

PLEASE CALL US AT (760) 710-0510